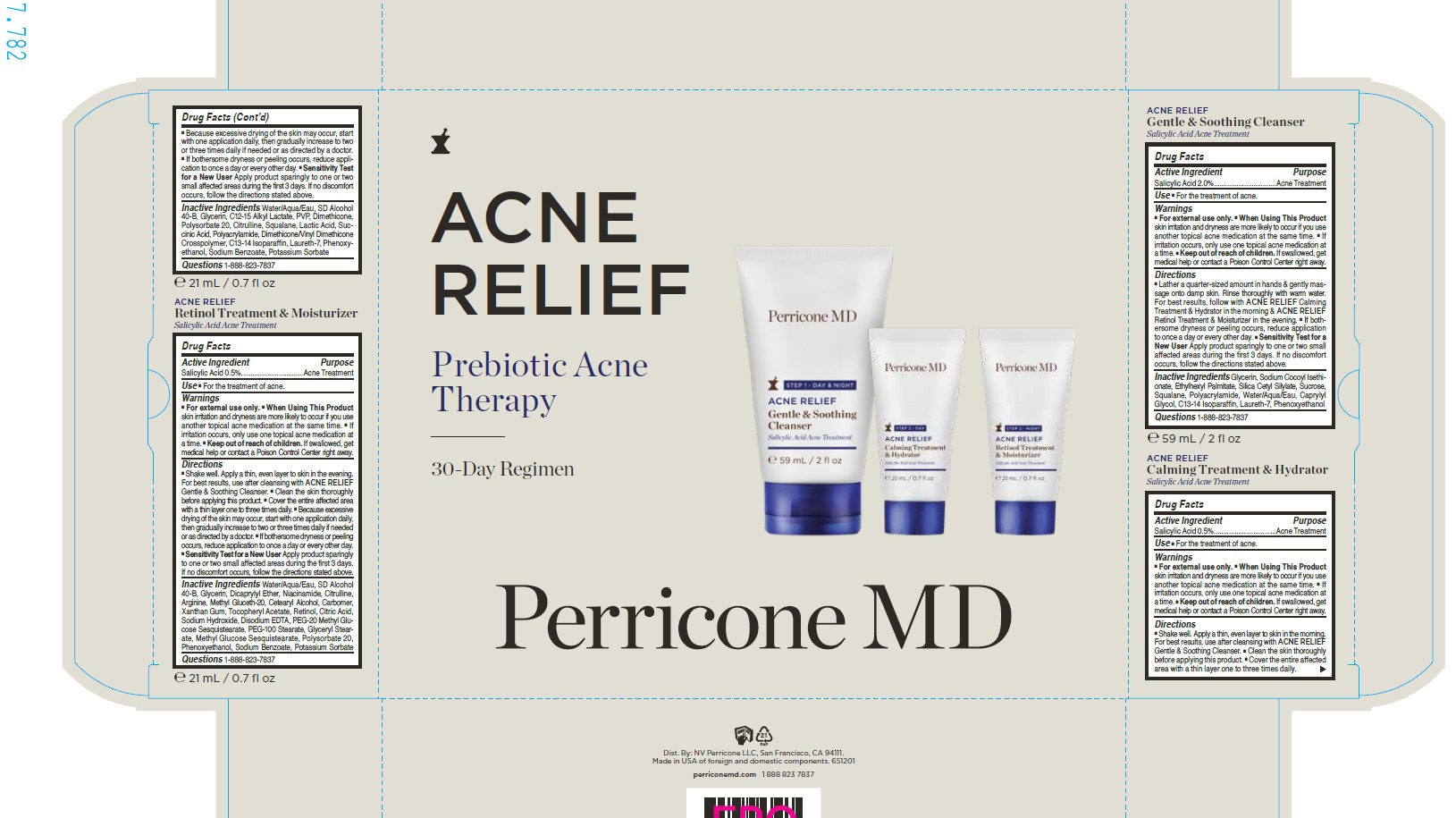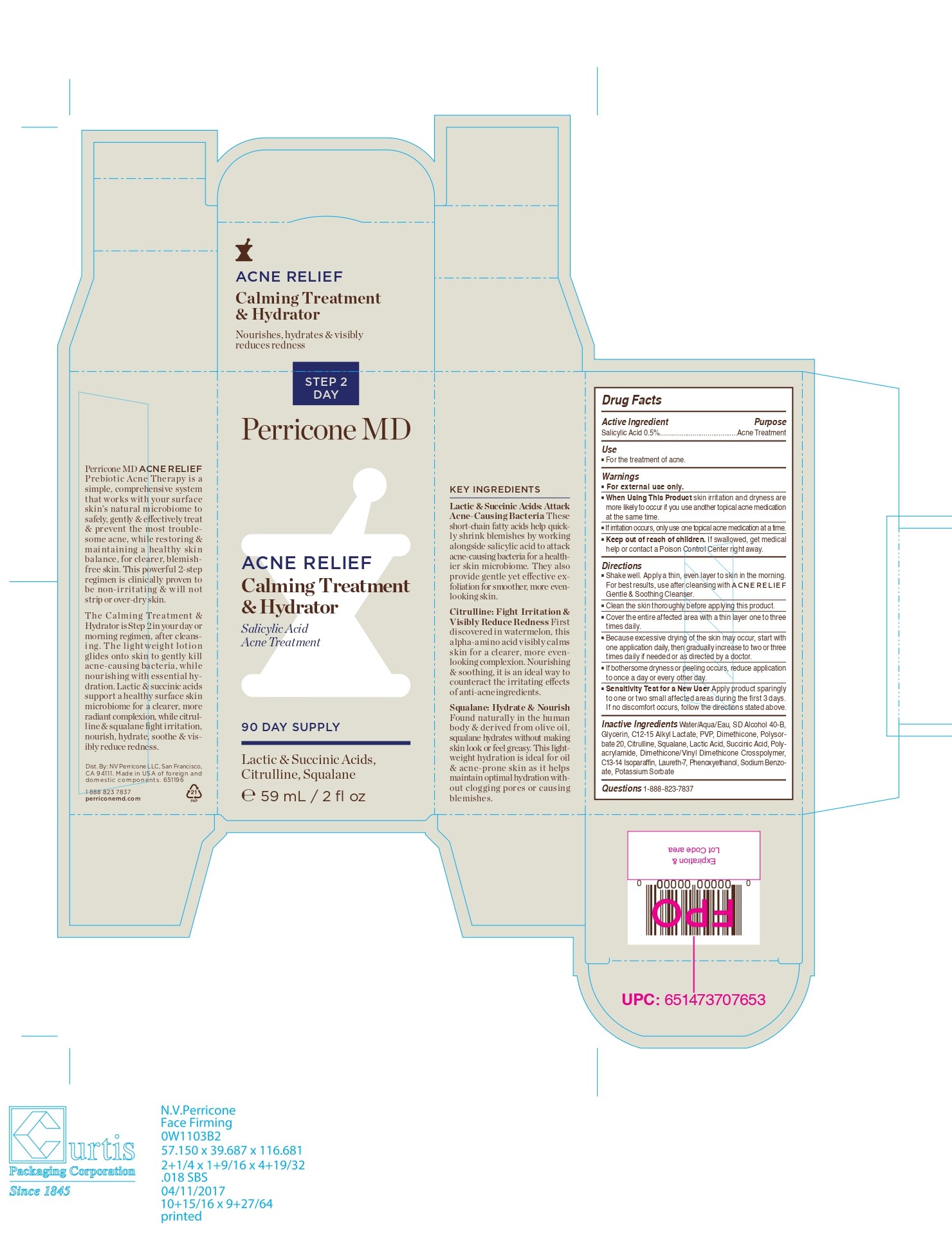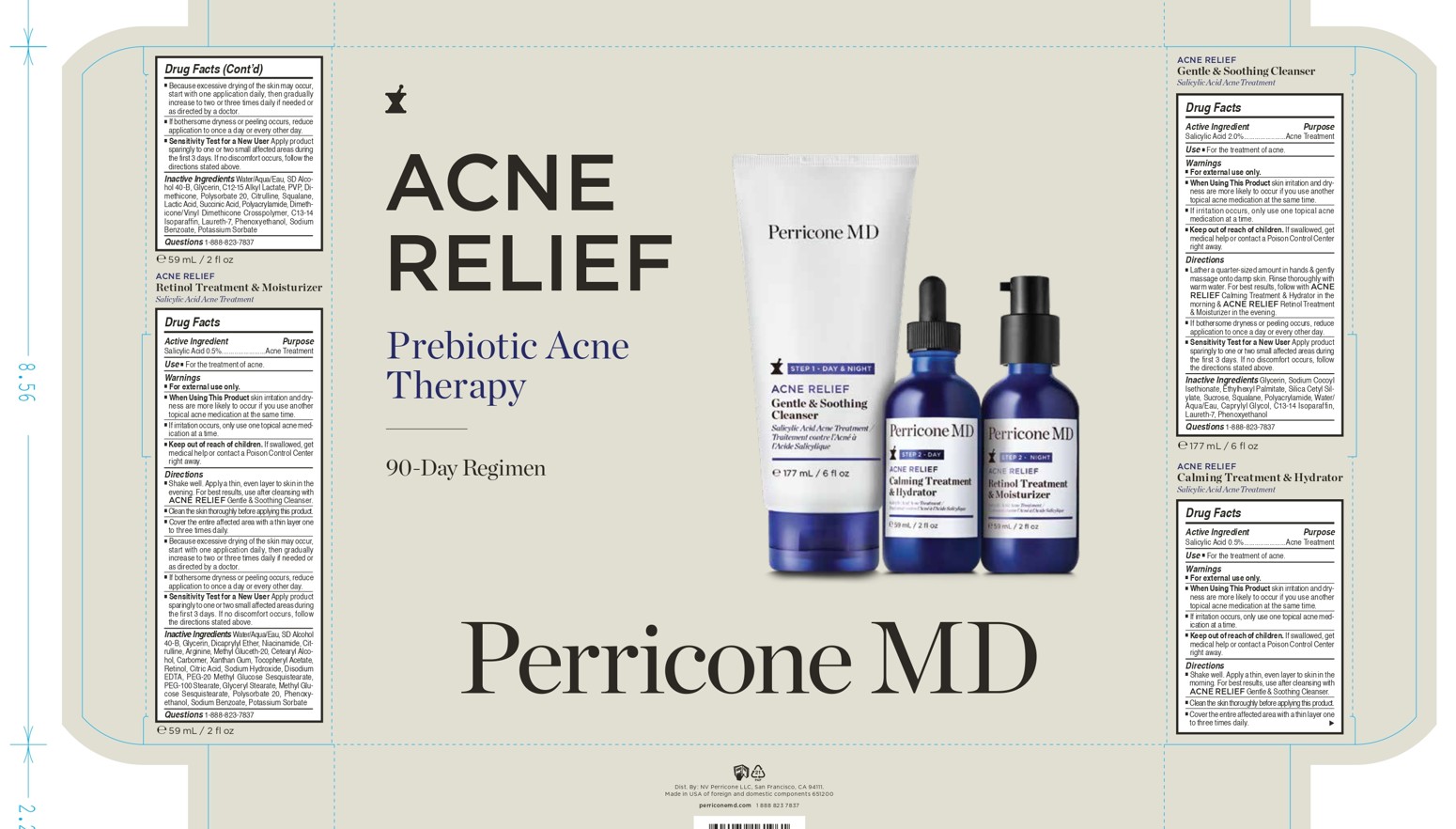 DRUG LABEL: Perricone MD Acne Relief Calming Treatment and Hydrator Salicylic Acid Acne Treatment
NDC: 84448-540 | Form: CREAM
Manufacturer: THG Beauty USA LLC
Category: otc | Type: HUMAN OTC DRUG LABEL
Date: 20251030

ACTIVE INGREDIENTS: SALICYLIC ACID 0.5 g/100 mL
INACTIVE INGREDIENTS: POLYSORBATE 20; PHENOXYETHANOL; SUCCINIC ACID; SODIUM BENZOATE; C12-15 ALKYL LACTATE; C13-14 ISOPARAFFIN; DIMETHICONE/VINYL DIMETHICONE CROSSPOLYMER (HARD PARTICLE); LACTIC ACID; LAURETH-7; CITRULLINE; SQUALANE; ALCOHOL; GLYCERIN; DIMETHICONE; WATER; POLYACRYLAMIDE (CROSSLINKED; 2 MOLE PERCENT BISACRYLAMIDE); POTASSIUM SORBATE; PVP

ACTIVE INGREDIENT

Salicylic Acid 0.5%

PURPOSE

Acne Treatment

INDICATIONS AND USAGE

■ For the treatment of acne

WARNINGS

- For external use only

When Using This Product skin irritation and dryness are
more likely to occur if you use another topical acne medication
at the same time.
■ If irritation occurs, only use one topical acne medication at a time

Keep out of reach of children. If swallowed, get medical
help or contact a Poison Control Center right away.

DOSAGE AND ADMINISTRATION

Directions ■ Shake well. Apply a thin, even layer to skin in the morning.
For best results, use after cleansing with ACNE RELIEF
Gentle & Soothing Cleanser.
■ Clean the skin thoroughly before applying this product. ■ Cover the entire affected area with a thin layer one to three
times daily.
■ Because excessive drying of the skin may occur, start with
one application daily, then gradually increase to two or three
times daily if needed or as directed by a doctor.
■ If bothersome dryness or peeling occurs, reduce application
to once a day or every other day.
■ Sensitivity Test for a New User Apply product sparingly
to one or two small affected areas during the first 3 days.
If no discomfort occurs, follow the directions sta

INACTIVE INGREDIENT

Water/Aqua/Eau, SD Alcohol 40-B, Glycerin, C12-15 Alkyl Lactate, PVP, Dimethicone, Polysorbate 20, Citrulline, Squalane, Lactic Acid, Succinic Acid, Polyacrylamide, Dimethicone/Vinyl Dimethicone Crosspolymer, C13-14 Isoparaffin, Laureth-7, Phenoxyethanol, Sodium Benzoate, Potassium Sorbate

QUESTIONS

1-888-823-7837